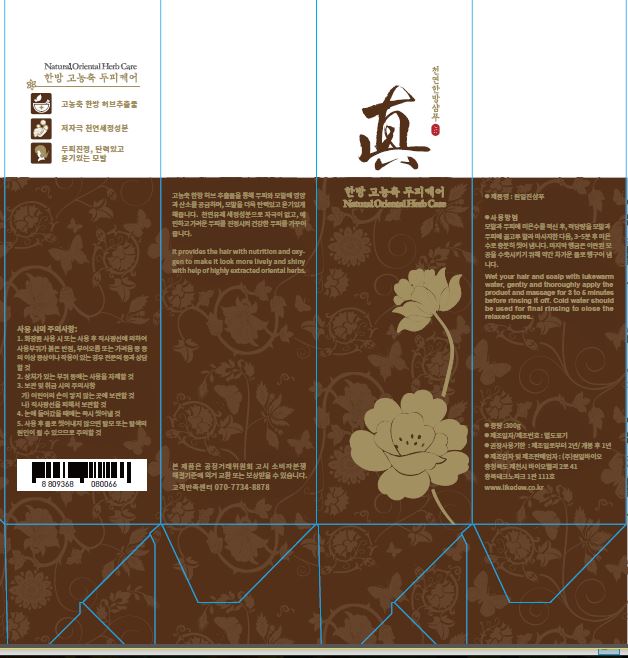 DRUG LABEL: Natural Oriental Herb Care
NDC: 71967-0001 | Form: SHAMPOO
Manufacturer: Wonilbio Inc
Category: otc | Type: HUMAN OTC DRUG LABEL
Date: 20171221

ACTIVE INGREDIENTS: BUTYLENE GLYCOL 1 g/100 g
INACTIVE INGREDIENTS: WATER

Drug Facts

ACTIVE INGREDIENT

butylene glycol

INACTIVE INGREDIENT

Aqua, Disodium Laureth Sulfosuccinate, Lauramidopropyl Betaine, PEG-120 Methyl Glucose Dioleate, Sodium chloride, Chrysanthellum Indicum Extract, Biota Orientalis Leaf Extract, Silk Amino Acids, Houttuynia Cordata Extract, Panthenol, Betaine, Hippophae Rhamnoides Extract, Rosmarinus Officinalis (Rosemary) Leaf Extract, Chitosan, Ulmus Davidiana Root Extract, Vitex Trifolia Fruit Extract, Citric Acid, Chamomilla Recutita (Matricaria) Flower/Leaf Extract, 1,2-Hexanediol, Cnidium Officinale Root Extract, Eclipta Prostrata Extract, Polygonum Multiflorum Root Extract, Isoamyl Laurate, Rosmarinus Officinalis (Rosemary) Leaf Oil, Butylene Glycol, Verbena Officinalis Extract, Polyquaternium-10, Saururus Chinensis Extract, Caprylyl Glycol, Morus Alba Bark Extract, Sodium Phytate, Lavandula Angustifolia (Lavender) Oil, Urtica Dioica (Nettle) Extract, Cananga Odorata Flower Oil

PURPOSE

for scalp care

KEEP OUT OF REACH OF THE CHILDREN

INDICATIONS AND USAGE

Wash off the scalp for cleansing when washing your hair first and leave on for about 5 minutes after creating foams on the hair with shampoo when washing your hair second.

Then, herbal extracts in the shampoo are absorbed into the scalp, which is soothed and supplied with nutrition more effectively.

WARNINGS

1. Do not use in the following cases(Eczema and scalp wounds)
2.Side Effects
1)Due to the use of this druf if rash, irritation, itching and symptopms of hypersnesitivity occur dicontinue use and consult your phamacisr or doctor
3.General Precautions
1)If in contact with the eyes, wash out thoroughty with water If the symptoms are servere, seek medical advice immediately
2)This product is for exeternal use only. Do not use for internal use
4.Storage and handling precautions
1)If possible, avoid direct sunlight and store in cool and area of low humidity
2)In order to maintain the quality of the product and avoid misuse
3)Avoid placing the product near fire and store out in reach of children

DOSAGE AND ADMINISTRATION

for external use only